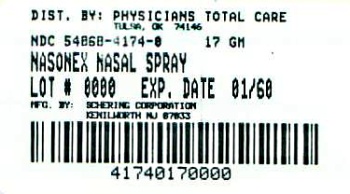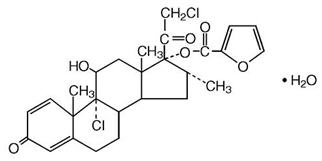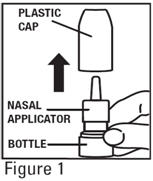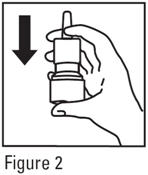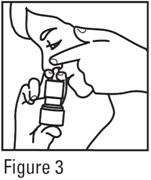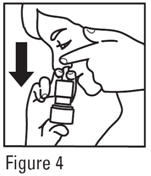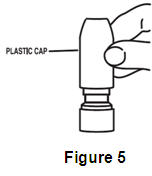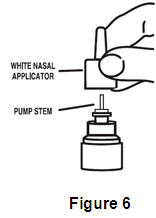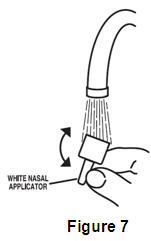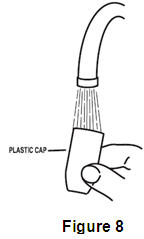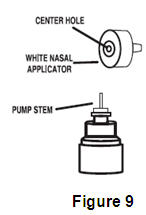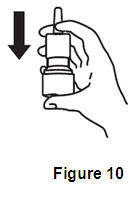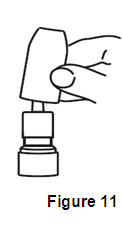 DRUG LABEL: NASONEX
NDC: 54868-4174 | Form: SPRAY, METERED
Manufacturer: Physicians Total Care, Inc.
Category: prescription | Type: HUMAN PRESCRIPTION DRUG LABEL
Date: 20110126

ACTIVE INGREDIENTS: MOMETASONE FUROATE 50 ug/1 1
INACTIVE INGREDIENTS: GLYCERIN; CELLULOSE, MICROCRYSTALLINE; CARBOXYMETHYLCELLULOSE SODIUM; SODIUM CITRATE; CITRIC ACID MONOHYDRATE; BENZALKONIUM CHLORIDE; POLYSORBATE 80

HIGHLIGHTS OF PRESCRIBING INFORMATION

These highlights do not include all the information needed to use NASONEX safely and effectively. See full prescribing information for NASONEX.
NASONEX® (mometasone furoate monohydrate) Nasal Spray 50 mcg†
†calculated on the anhydrous basis
Initial U.S. Approval: 1997

1. INDICATIONS AND USAGE

NASONEX is a corticosteroid indicated for:

1. Treatment of Nasal Symptoms of Allergic Rhinitis in patients ≥2 years of age (1.1)
2. Treatment of Nasal Congestion Associated with Seasonal Allergic Rhinitis in patients ≥2 years of age (1.2)
3. Prophylaxis of Seasonal Allergic Rhinitis in patients ≥12 years of age (1.3)
4. Treatment of Nasal Polyps in patients ≥18 years of age (1.4)

2. DOSAGE AND ADMINISTRATION

For Intranasal Use Only

- Treatment of Nasal Symptoms of Allergic Rhinitis (2.1)
  Adults & Adolescents (12 yrs. and older): 2 sprays in each nostril once daily
  Children (2–11 yrs.): 1 spray in each nostril once daily
- Treatment of Nasal Congestion Associated with Seasonal Allergic Rhinitis (2.2)
  Adults & Adolescents (12 yrs. and older): 2 sprays in each nostril once daily
  Children (2–11 yrs.): 1 spray in each nostril once daily
- Prophylaxis of Seasonal Allergic Rhinitis (2.3)
  Adults & Adolescents (12 yrs. and older): 2 sprays in each nostril once daily
- Treatment of Nasal Polyps (2.4)

Adults (18 yrs. and older): 2 sprays in each nostril twice daily. 2 sprays in each nostril once daily may also be effective in some patients.

3. DOSAGE FORMS AND STRENGTHS

Nasal Spray: 50 mcg of mometasone furoate in each 100-microliter spray (3)

4. CONTRAINDICATIONS

Patients with known hypersensitivity to mometasone furoate or any of the ingredients of NASONEX. (4)

5. WARNINGS AND PRECAUTIONS

- Epistaxis, nasal ulceration, Candida albicans infection, nasal septal perforation, impaired wound healing. Monitor patients periodically for signs of adverse effects on the nasal mucosa. Avoid use in patients with recent nasal ulcers, nasal surgery, or nasal trauma. (5.1)
- Development of glaucoma or cataracts. Monitor patients closely with a change in vision or with a history of increased intraocular pressure, glaucoma, and/or cataracts. (5.2)
- Potential worsening of existing tuberculosis; fungal, bacterial, viral, or parasitic infections; or ocular herpes simplex. More serious or even fatal course of chickenpox or measles in susceptible patients. Use caution in patients with the above because of the potential for worsening of these infections. (5.4)
- Hypercorticism and adrenal suppression with higher than recommended dosages or at the regular dosage in susceptible individuals. If such changes occur, discontinue NASONEX Nasal Spray slowly. (5.5)
- Potential reduction in growth velocity in children. Monitor growth routinely in pediatric patients receiving NASONEX Nasal Spray. (5.6, 8.4)

6. ADVERSE REACTIONS

The most common adverse reactions (≥5%) included headache, viral infection, pharyngitis, epistaxis and cough. (6)

To report SUSPECTED ADVERSE REACTIONS, contact Schering Corporation, a subsidiary of Merck & Co., Inc., at 1- 800-526-4099 or FDA at 1-800-FDA-1088 or www.fda.gov/medwatch.

FULL PRESCRIBING INFORMATION

1. INDICATIONS AND USAGE

1.1 Treatment of Allergic Rhinitis

NASONEX® Nasal Spray 50 mcg is indicated for the treatment of the nasal symptoms of seasonal allergic and perennial allergic rhinitis, in adults and pediatric patients 2 years of age and older.

1.2 Treatment of Nasal Congestion Associated with Seasonal Allergic Rhinitis

NASONEX Nasal Spray 50 mcg is indicated for the relief of nasal congestion associated with seasonal allergic rhinitis, in adults and pediatric patients 2 years of age and older.

1.3 Prophylaxis of Seasonal Allergic Rhinitis

NASONEX Nasal Spray 50 mcg is indicated for the prophylaxis of the nasal symptoms of seasonal allergic rhinitis in adult and adolescent patients 12 years and older.

1.4 Treatment of Nasal Polyps

NASONEX Nasal Spray 50 mcg is indicated for the treatment of nasal polyps in patients 18 years of age and older.

2. DOSAGE AND ADMINISTRATION

Administer NASONEX Nasal Spray 50 mcg by the intranasal route only. Prior to initial use of NASONEX Nasal Spray, 50 mcg, the pump must be primed by actuating ten times or until a fine spray appears. The pump may be stored unused for up to 1 week without repriming. If unused for more than 1 week, reprime by actuating two times, or until a fine spray appears.

2.1 Treatment of Allergic Rhinitis

Adults and Adolescents 12 Years of Age and Older:

The recommended dose for treatment of the nasal symptoms of seasonal allergic and perennial allergic rhinitis is 2 sprays (50 mcg of mometasone furoate in each spray) in each nostril once daily (total daily dose of 200 mcg).

Children 2 to 11 Years of Age:

The recommended dose for treatment of the nasal symptoms of seasonal allergic and perennial allergic rhinitis is 1 spray (50 mcg of mometasone furoate in each spray) in each nostril once daily (total daily dose of 100 mcg).

2.2 Treatment of Nasal Congestion Associated with Seasonal Allergic Rhinitis

Adults and Adolescents 12 Years of Age and Older:

The recommended dose for treatment of nasal congestion associated with seasonal allergic rhinitis is two sprays (50 mcg of mometasone furoate in each spray) in each nostril once daily (total daily dose of 200 mcg).

Children 2 to 11 Years of Age:

The recommended dose for treatment of nasal congestion associated with seasonal allergic rhinitis is one spray (50 mcg of mometasone furoate in each spray) in each nostril once daily (total daily dose of 100 mcg).

2.3 Prophylaxis of Seasonal Allergic Rhinitis

Adults and Adolescents 12 Years of Age and Older:

The recommended dose for prophylaxis treatment of nasal symptoms of seasonal allergic rhinitis is 2 sprays (50 mcg of mometasone furoate in each spray) in each nostril once daily (total daily dose of 200 mcg).

In patients with a known seasonal allergen that precipitates nasal symptoms of seasonal allergic rhinitis, prophylaxis with NASONEX Nasal Spray 50 mcg (200 mcg/day) is recommended 2 to 4 weeks prior to the anticipated start of the pollen season.

2.4 Treatment of Nasal Polyps

Adults 18 Years of Age and Older:

The recommended dose for the treatment of nasal polyps is 2 sprays (50 mcg of mometasone furoate in each spray) in each nostril twice daily (total daily dose of 400 mcg). A dose of 2 sprays (50 mcg of mometasone furoate in each spray) in each nostril once daily (total daily dose of 200 mcg) is also effective in some patients.

3. DOSAGE FORMS AND STRENGTHS

NASONEX Nasal Spray 50 mcg is a metered-dose, manual pump spray unit containing an aqueous suspension of mometasone furoate monohydrate equivalent to 0.05% w/w mometasone furoate calculated on the anhydrous basis.

After initial priming (10 actuations), each actuation of the pump delivers a metered spray containing 100 mg or 100 microliter of suspension containing mometasone furoate monohydrate equivalent to 50 mcg of mometasone furoate calculated on the anhydrous basis. Each bottle of NASONEX Nasal Spray 50 mcg provides 120 sprays.

4. CONTRAINDICATIONS

NASONEX Nasal Spray is contraindicated in patients with known hypersensitivity to mometasone furoate or any of its ingredients.

5. WARNINGS AND PRECAUTIONS

5.1 Local Nasal Effects

Epistaxis

In clinical studies, epistaxis was observed more frequently in patients with allergic rhinitis with NASONEX Nasal Spray than those who received placebo [see Adverse Reactions (6)].

Candida Infection

In clinical studies with NASONEX Nasal Spray 50 mcg, the development of localized infections of the nose and pharynx with Candida albicans has occurred. When such an infection develops, use of NASONEX Nasal Spray 50 mcg should be discontinued and appropriate local or systemic therapy instituted, if needed.

Nasal Septum Perforation

Instances of nasal septum perforation have been reported following the intranasal application of corticosteroids. As with any long-term topical treatment of the nasal cavity, patients using NASONEX Nasal Spray 50 mcg over several months or longer should be examined periodically for possible changes in the nasal mucosa.

Impaired Wound Healing

Because of the inhibitory effect of corticosteroids on wound healing, patients who have experienced recent nasal septum ulcers, nasal surgery, or nasal trauma should not use a nasal corticosteroid until healing has occurred.

5.2 Glaucoma and Cataracts

Nasal and inhaled corticosteroids may result in the development of glaucoma and/or cataracts. Therefore, close monitoring is warranted in patients with a change in vision or with a history of increased intraocular pressure, glaucoma, and/or cataracts.

Glaucoma and cataract formation was evaluated in one controlled study of 12 weeks' duration and one uncontrolled study of 12 months' duration in patients treated with NASONEX Nasal Spray, 50 mcg at 200 mcg/day, using intraocular pressure measurements and slit lamp examination. No significant change from baseline was noted in the mean intraocular pressure measurements for the 141 NASONEX-treated patients in the 12-week study, as compared with 141 placebo-treated patients. No individual NASONEX-treated patient was noted to have developed a significant elevation in intraocular pressure or cataracts in this 12-week study. Likewise, no significant change from baseline was noted in the mean intraocular pressure measurements for the 139 NASONEX-treated patients in the 12-month study and again, no cataracts were detected in these patients. Nonetheless, nasal and inhaled corticosteroids have been associated with the development of glaucoma and/or cataracts.

5.3 Hypersensitivity Reactions

Hypersensitivity reactions including instances of wheezing may occur after the intranasal administration of mometasone furoate monohydrate. Discontinue Nasonex Nasal Spray if such reactions occur [see Contraindications (4)].

5.4 Immunosuppression

Persons who are on drugs which suppress the immune system are more susceptible to infections than healthy individuals. Chickenpox and measles, for example, can have a more serious or even fatal course in nonimmune children or adults on corticosteroids. In such children or adults who have not had these diseases, particular care should be taken to avoid exposure. How the dose, route, and duration of corticosteroid administration affect the risk of developing a disseminated infection is not known. The contribution of the underlying disease and/or prior corticosteroid treatment to the risk is also not known. If exposed to chickenpox, prophylaxis with varicella zoster immune globin (VZIG) may be indicated. If exposed to measles, prophylaxis with pooled intramuscular immunoglobulin (IG) may be indicated. (See the respective package inserts for complete VZIG and IG prescribing information.) If chickenpox develops, treatment with antiviral agents may be considered.

Corticosteroids should be used with caution, if at all, in patients with active or quiescent tuberculous infection of the respiratory tract, or in untreated fungal, bacterial, systemic viral infections, or ocular herpes simplex because of the potential for worsening of these infections.

5.5 Hypothalamic-Pituitary-Adrenal Axis Effect

Hypercorticism and Adrenal Suppression

When intranasal steroids are used at higher than recommended dosages or in susceptible individuals at recommended dosages, systemic corticosteroid effects such as hypercorticism and adrenal suppression may appear. If such changes occur, the dosage of Nasonex Nasal Spray should be discontinued slowly, consistent with accepted procedures for discontinuing oral corticosteroid therapy.

5.6 Effect on Growth

Corticosteroids may cause a reduction in growth velocity when administered to pediatric patients. Monitor the growth routinely of pediatric patients receiving NASONEX Nasal Spray. To minimize the systemic effects of intranasal corticosteroids, including NASONEX Nasal Spray, titrate each patient's dose to the lowest dosage that effectively controls his/her symptoms [see Use in Specific Populations (8.4)].

6. ADVERSE REACTIONS

Systemic and local corticosteroid use may result in the following:

- Epistaxis, ulcerations, Candida albicans infection, impaired wound healing [see Warnings and Precautions (5.1)]
- Cataracts and glaucoma [see Warnings and Precautions (5.2)]
- Immunosuppression [see Warnings and Precautions (5.4)]
- Hypothalamic-pituitary-adrenal (HPA) axis effects, including growth reduction [see Warnings and Precautions (5.5, 5.6), Use in Specific Populations (8.4)]

6.1 Clinical Trials Experience

Because clinical trials are conducted under widely varying conditions, adverse reaction rates observed in the clinical trials of a drug cannot be directly compared to rates in the clinical trials of another drug and may not reflect the rates observed in practice.

Allergic Rhinitis

Adults and adolescents 12 years of age and older

In controlled US and international clinical studies, a total of 3210 adult and adolescent patients 12 years and older with allergic rhinitis received treatment with NASONEX Nasal Spray 50 mcg at doses of 50 to 800 mcg/day. The majority of patients (n = 2103) were treated with 200 mcg/day. A total of 350 adult and adolescent patients have been treated for one year or longer. Adverse events did not differ significantly based on age, sex, or race. Four percent or less of patients in clinical trials discontinued treatment because of adverse events and the discontinuation rate was similar for the vehicle and active comparators.

All adverse events (regardless of relationship to treatment) reported by 5% or more of adult and adolescent patients ages 12 years and older who received NASONEX Nasal Spray 50 mcg, 200 mcg/day vs. placebo and that were more common with NASONEX Nasal Spray 50 mcg than placebo, are displayed in TABLE 1 below.

TABLE 1: ADULT AND ADOLESCENT PATIENTS 12 YEARS AND OLDER – ADVERSE EVENTS FROM CONTROLLED CLINICAL TRIALS IN SEASONAL ALLERGIC AND PERENNIAL ALLERGIC RHINITIS (PERCENT OF PATIENTS REPORTING)
 | NASONEX 200 mcg (n = 2103) | VEHICLE PLACEBO (n = 1671)
Headache | 26 | 22
Viral Infection | 14 | 11
Pharyngitis | 12 | 10
Epistaxis/Blood-Tinged Mucus | 11 | 6
Coughing | 7 | 6
Upper Respiratory Tract Infection | 6 | 2
Dysmenorrhea | 5 | 3
Musculoskeletal Pain | 5 | 3
Sinusitis | 5 | 3

Other adverse events which occurred in less than 5% but greater than or equal to 2% of adult and adolescent patients (ages 12 years and older) treated with NASONEX Nasal Spray 50 mcg, 200-mcg/day (regardless of relationship to treatment), and more frequently than in the placebo group included: arthralgia, asthma, bronchitis, chest pain, conjunctivitis, diarrhea, dyspepsia, earache, flu-like symptoms, myalgia, nausea, and rhinitis.

Pediatric patients <12 years of age

In controlled US and international studies, a total of 990 pediatric patients (ages 3 to 11 years) with allergic rhinitis received treatment with NASONEX Nasal Spray 50 mcg, at doses of 25 to 200 mcg/day. The majority of pediatric patients (n = 720) were treated with 100 mcg/day. A total of 163 pediatric patients have been treated for one year or longer. Two percent or less of patients in clinical trials who received NASONEX Nasal Spray 50 mcg discontinued treatment because of adverse events and the discontinuation rate was similar for the placebo and active comparators.

Adverse events which occurred in ≥5% of pediatric patients (ages 3 to 11 years) treated with NASONEX Nasal Spray 50 mcg, 100 mcg/day vs. placebo (regardless of relationship to treatment) and more frequently than in the placebo group included upper respiratory tract infection (5% in NASONEX Nasal Spray 50 mcg group vs. 4% in placebo) and vomiting (5% in NASONEX Nasal Spray 50 mcg group vs. 4% in placebo).

Other adverse events which occurred in less than 5% but greater than or equal to 2% of pediatric patients (ages 3 to 11 years) treated NASONEX Nasal Spray 50 mcg, 100 mcg/day vs. placebo (regardless of relationship to treatment) and more frequently than in the placebo group included: diarrhea, nasal irritation, otitis media, and wheezing.

The adverse event (regardless of relationship to treatment) reported by 5% of pediatric patients ages 2 to 5 years who received NASONEX Nasal Spray, 50 mcg, 100 mcg/day in a clinical trial vs. placebo including 56 subjects (28 each NASONEX Nasal Spray, 50 mcg and placebo) and that was more common with NASONEX Nasal Spray, 50 mcg than placebo, included: upper respiratory tract infection (7% vs. 0%, respectively). The other adverse event which occurred in less than 5% but greater than or equal to 2% of mometasone furoate pediatric patients ages 2 to 5 years treated with 100 mcg doses vs. placebo (regardless of relationship to treatment) and more frequently than in the placebo group included: skin trauma.

Nasal Polyps

Adults 18 years of age and older

In controlled clinical studies, the types of adverse events observed in patients with nasal polyps were similar to those observed for patients with allergic rhinitis. A total of 594 adult patients (ages 18 to 86 years) received NASONEX Nasal Spray 50 mcg at doses of 200 mcg once or twice daily for up to 4 months for treatment of nasal polyps. The overall incidence of adverse events for patients treated with NASONEX Nasal Spray 50 mcg was comparable to patients with the placebo except for epistaxis, which was 9% for 200 mcg once daily, 13% for 200 mcg twice daily, and 5% for the placebo.

Nasal ulcers and nasal and oral candidiasis were also reported in patients treated with NASONEX Nasal Spray 50 mcg primarily in patients treated for longer than 4 weeks.

Nasal Congestion Associated with Seasonal Allergic Rhinitis

A total of 1008 patients aged 12 years and older received NASONEX Nasal Spray 50 mcg 200 mcg/day (n = 506) or placebo (n = 502) for 15 days. Adverse events that occurred more frequently in patients treated with NASONEX Nasal Spray 50 mcg than in patients with the placebo included sinus headache (1.2% in NASONEX Nasal Spray 50 mcg group vs. 0.2% in placebo) and epistaxis (1% in NASONEX Nasal Spray 50 mcg group vs. 0.2% in placebo) and the overall adverse event profile was similar to that observed in the other allergic rhinitis trials.

6.2 Post-Marketing Experience

The following adverse reactions have been identified during the post-marketing period for NASONEX Nasal Spray 50 mcg: nasal burning and irritation, anaphylaxis and angioedema, disturbances in taste and smell and nasal septal perforation. Because these reactions are reported voluntarily from a population of uncertain size, it is not always possible to reliably estimate their frequency or establish a causal relationship to drug exposure.

7. DRUG INTERACTIONS

No formal drug-drug interaction studies have been conducted with NASONEX Nasal Spray 50 mcg.

Inhibitors of Cytochrome P450 3A4: Studies have shown that mometasone furoate is primarily and extensively metabolized in the liver of all species investigated and undergoes extensive metabolism to multiple metabolites. In vitro studies have confirmed the primary role of cytochrome CYP 3A4 in the metabolism of this compound. Coadministration with ketoconazole, a potent CYP 3A4 inhibitor, may increase the plasma concentrations of mometasone furoate [see Clinical Pharmacology (12.3)].

8. USE IN SPECIFIC POPULATIONS

8.1 Pregnancy

TERATOGENIC EFFECTS

Teratogenic Effects: Pregnancy Category C: There are no adequate and well-controlled studies in pregnant women. NASONEX Nasal Spray 50 mcg, like other corticosteroids, should be used during pregnancy only if the potential benefits justify the potential risk to the fetus. Experience with oral corticosteroids since their introduction in pharmacologic, as opposed to physiologic, doses suggests that rodents are more prone to teratogenic effects from corticosteroids than humans. In addition, because there is a natural increase in corticosteroid production during pregnancy, most women will require a lower exogenous corticosteroid dose and many will not need corticosteroid treatment during pregnancy.

In mice, mometasone furoate caused cleft palate at subcutaneous doses (less than the MRDID in adults on a mcg/m^2 basis). Fetal survival was reduced at approximately 2 times the MRDID in adults on a mcg/m^2 basis. No toxicity was observed at less than the MRDID in adults on a mcg/m^2 basis.

In rats, mometasone furoate produced umbilical hernia at topical dermal doses approximately 10 times the MRDID in adults on a mcg/m^2 basis. A topical dermal dose approximately 6 times the MRDID in adults on a mcg/m^2 basis produced delays in ossification, but no malformations.

In rabbits, mometasone furoate caused multiple malformations (e.g., flexed front paws, gallbladder agenesis, umbilical hernia, and hydrocephaly) at topical dermal doses approximately 6 times the MRDID in adults on a mcg/m^2 basis. In an oral study, mometasone furoate increased resorptions and caused cleft palate and/or head malformations (hydrocephaly or domed head) at approximately 30 times the MRDID in adults on a mcg/m^2 basis. At approximately 110 times the MRDID in adults on a mcg/m^2 basis, most litters were aborted or resorbed. No toxicity was observed at approximately 6 times the MRDID in adults on a mcg/m^2 basis.

When rats received subcutaneous doses of mometasone furoate throughout pregnancy or during the later stages of pregnancy, a dose less than the MRDID in adults on a mcg/m^2 basis caused prolonged and difficult labor and reduced the number of live births, birth weight, and early pup survival.

NONTERATOGENIC EFFECTS

Nonteratogenic Effects: Hypoadrenalism may occur in infants born to women receiving corticosteroids during pregnancy. Such infants should be carefully monitored.

8.3 Nursing Mothers

It is not known if mometasone furoate is excreted in human milk. Because other corticosteroids are excreted in human milk, caution should be used when NASONEX Nasal Spray, 50 mcg is administered to nursing women.

8.4 Pediatric Use

The safety and effectiveness of NASONEX Nasal Spray 50 mcg for allergic rhinitis in children 12 years of age and older have been established [see Adverse Reactions (6.1) and Clinical Studies (14.1)]. Use of NASONEX Nasal Spray 50 mcg for allergic rhinitis in pediatric patients 2 to 11 years of age is supported by safety and efficacy data from clinical studies. Seven hundred and twenty (720) patients 3 to 11 years of age with allergic rhinitis were treated with mometasone furoate nasal spray 50 mcg (100 mcg total daily dose) in controlled clinical trials [see Adverse Reactions (6.1) and Clinical Studies (14.2)]. Twenty-eight (28) patients 2 to 5 years of age with allergic rhinitis were treated with mometasone furoate nasal spray 50 mcg (100 mcg total daily dose) in a controlled trial to evaluate safety [see Adverse Reactions (6.1)]. Safety and effectiveness of Nasonex Nasal Spray 50 mcg for allergic rhinitis in children less than 2 years of age have not been established.

The safety and effectiveness of Nasonex Nasal Spray for the treatment of nasal polyps in children less than 18 years of age have not been established. One 4-month trial was conducted to evaluate the safety and efficacy of Nasonex in the treatment of nasal polyps in pediatric patients 6 to 17 years of age. The primary objective of the study was to evaluate safety; efficacy parameters were collected as secondary endpoints. A total of 127 patients with nasal polyps were randomized to placebo or Nasonex Nasal Spray 100 mcg once or twice daily (patients 6 to 11 years of age) or 200 mcg once or twice daily (patients 12 to 17 years of age). The results of this trial did not support the efficacy of Nasonex Nasal Spray in the treatment of nasal polyps in pediatric patients. The adverse events reported in this trial were similar to the adverse events reported in patients 18 years of age and older with nasal polyps.

Controlled clinical studies have shown intranasal corticosteroids may cause a reduction in growth velocity in pediatric patients. This effect has been observed in the absence of laboratory evidence of hypothalamic-pituitary-adrenal (HPA) axis suppression, suggesting that growth velocity is a more sensitive indicator of systemic corticosteroid exposure in pediatric patients than some commonly used tests of HPA axis function. The long-term effects of this reduction in growth velocity associated with intranasal corticosteroids, including the impact on final adult height, are unknown. The potential for "catch up" growth following discontinuation of treatment with intranasal corticosteroids has not been adequately studied. The growth of pediatric patients receiving intranasal corticosteroids, including NASONEX Nasal Spray, 50 mcg, should be monitored routinely (e.g., via stadiometry). The potential growth effects of prolonged treatment should be weighed against clinical benefits obtained and the availability of safe and effective noncorticosteroid treatment alternatives. To minimize the systemic effects of intranasal corticosteroids, including NASONEX Nasal Spray, 50 mcg, each patient should be titrated to his/her lowest effective dose.

A clinical study to assess the effect of NASONEX Nasal Spray 50 mcg (100 mcg total daily dose) on growth velocity has been conducted in pediatric patients 3 to 9 years of age with allergic rhinitis. No statistically significant effect on growth velocity was observed for NASONEX Nasal Spray 50 mcg compared to placebo following one year of treatment. No evidence of clinically relevant HPA axis suppression was observed following a 30-minute cosyntropin infusion.

The potential of NASONEX Nasal Spray 50 mcg to cause growth suppression in susceptible patients or when given at higher doses cannot be ruled out.

8.5 Geriatric Use

A total of 280 patients above 64 years of age with allergic rhinitis or nasal polyps (age range 64 to 86 years) have been treated with NASONEX Nasal Spray 50 mcg for up to 3 or 4 months, respectively. The adverse reactions reported in this population were similar in type and incidence to those reported by younger patients.

8.6 Hepatic Impairment

Concentrations of mometasone furoate appear to increase with severity of hepatic impairment [see Clinical Pharmacology (12.3)]

10. OVERDOSAGE

There are no data available on the effects of acute or chronic overdosage with NASONEX Nasal Spray 50 mcg. Because of low systemic bioavailability, and an absence of acute drug-related systemic findings in clinical studies, overdose is unlikely to require any therapy other than observation. Intranasal administration of 1600 mcg (4 times the recommended dose of NASONEX Nasal Spray 50 mcg for the treatment of nasal polyps in patients 18 years of age and older) daily for 29 days, to healthy human volunteers, showed no increased incidence of adverse events. Single intranasal doses up to 4000 mcg and oral inhalation doses up to 8000 mcg have been studied in human volunteers with no adverse effects reported. Chronic over dosage with any corticosteroid may result in signs or symptoms of hypercorticism [see Warnings and Precautions (5.4)]. Acute overdosage with this dosage form is unlikely since one bottle of NASONEX Nasal Spray 50 mcg contains approximately 8500 mcg of mometasone furoate.

11. DESCRIPTION

Mometasone furoate monohydrate, the active component of NASONEX Nasal Spray, 50 mcg, is an anti-inflammatory corticosteroid having the chemical name, 9,21-Dichloro-11ß,17-dihydroxy-16α-methylpregna-1,4-diene-3,20-dione17-(2 furoate) monohydrate, and the following chemical structure:

Mometasone furoate monohydrate is a white powder, with an empirical formula of C27H30Cl2O6•H2O, and a molecular weight of 539.45. It is practically insoluble in water; slightly soluble in methanol, ethanol, and isopropanol; soluble in acetone and chloroform; and freely soluble in tetrahydrofuran. Its partition coefficient between octanol and water is greater than 5000.

NASONEX Nasal Spray 50 mcg is a metered-dose, manual pump spray unit containing an aqueous suspension of mometasone furoate monohydrate equivalent to 0.05% w/w mometasone furoate calculated on the anhydrous basis; in an aqueous medium containing glycerin, microcrystalline cellulose and carboxymethylcellulose sodium, sodium citrate, citric acid, benzalkonium chloride, and polysorbate 80. The pH is between 4.3 and 4.9.

12. CLINICAL PHARMACOLOGY

12.1 Mechanism of Action

NASONEX Nasal Spray 50 mcg is a corticosteroid demonstrating potent anti-inflammatory properties. The precise mechanism of corticosteroid action on allergic rhinitis is not known. Corticosteroids have been shown to have a wide range of effects on multiple cell types (e.g., mast cells, eosinophils, neutrophils, macrophages, and lymphocytes) and mediators (e.g., histamine, eicosanoids, leukotrienes, and cytokines) involved in inflammation.

In two clinical studies utilizing nasal antigen challenge, NASONEX Nasal Spray, 50 mcg decreased some markers of the early- and late-phase allergic response. These observations included decreases (vs. placebo) in histamine and eosinophil cationic protein levels, and reductions (vs. baseline) in eosinophils, neutrophils, and epithelial cell adhesion proteins. The clinical significance of these findings is not known.

The effect of NASONEX Nasal Spray, 50 mcg on nasal mucosa following 12 months of treatment was examined in 46 patients with allergic rhinitis. There was no evidence of atrophy and there was a marked reduction in intraepithelial eosinophilia and inflammatory cell infiltration (e.g., eosinophils, lymphocytes, monocytes, neutrophils, and plasma cells).

12.2 Pharmacodynamics

Adrenal Function in Adults: Four clinical pharmacology studies have been conducted in humans to assess the effect of NASONEX Nasal Spray, 50 mcg at various doses on adrenal function. In one study, daily doses of 200 and 400 mcg of NASONEX Nasal Spray, 50 mcg and 10 mg of prednisone were compared to placebo in 64 patients (22 to 44 years of age) with allergic rhinitis. Adrenal function before and after 36 consecutive days of treatment was assessed by measuring plasma cortisol levels following a 6-hour Cortrosyn (ACTH) infusion and by measuring 24-hour urinary free cortisol levels. NASONEX Nasal Spray, 50 mcg, at both the 200- and 400-mcg dose, was not associated with a statistically significant decrease in mean plasma cortisol levels post-Cortrosyn infusion or a statistically significant decrease in the 24-hour urinary free cortisol levels compared to placebo. A statistically significant decrease in the mean plasma cortisol levels post-Cortrosyn infusion and 24-hour urinary free cortisol levels was detected in the prednisone treatment group compared to placebo.

A second study assessed adrenal response to NASONEX Nasal Spray, 50 mcg (400 and 1600 mcg/day), prednisone (10 mg/day), and placebo, administered for 29 days in 48 male volunteers (21 to 40 years of age). The 24-hour plasma cortisol area under the curve (AUC0–24), during and after an 8-hour Cortrosyn infusion and 24-hour urinary free cortisol levels were determined at baseline and after 29 days of treatment. No statistically significant differences in adrenal function were observed with NASONEX Nasal Spray, 50 mcg compared to placebo.

A third study evaluated single, rising doses of NASONEX Nasal Spray, 50 mcg (1000, 2000, and 4000 mcg/day), orally administered mometasone furoate (2000, 4000, and 8000 mcg/day), orally administered dexamethasone (200, 400, and 800 mcg/day), and placebo (administered at the end of each series of doses) in 24 male volunteers (22 to 39 years of age). Dose administrations were separated by at least 72 hours. Determination of serial plasma cortisol levels at 8 AM and for the 24-hour period following each treatment were used to calculate the plasma cortisol area under the curve (AUC0–24). In addition, 24-hour urinary free cortisol levels were collected prior to initial treatment administration and during the period immediately following each dose. No statistically significant decreases in the plasma cortisol AUC, 8 AM cortisol levels, or 24-hour urinary free cortisol levels were observed in volunteers treated with either NASONEX Nasal Spray, 50 mcg or oral mometasone, as compared with placebo treatment. Conversely, nearly all volunteers treated with the three doses of dexamethasone demonstrated abnormal 8 AM cortisol levels (defined as a cortisol level <10 mcg/dL), reduced 24-hour plasma AUC values, and decreased 24-hour urinary free cortisol levels, as compared to placebo treatment.

In a fourth study, adrenal function was assessed in 213 patients (18 to 81 years of age) with nasal polyps before and after 4 months of treatment with either NASONEX Nasal Spray, 50 mcg, (200 mcg once or twice daily) or placebo by measuring 24-hour urinary free cortisol levels. NASONEX Nasal Spray, 50 mcg, at both doses (200 and 400 mcg/day), was not associated with statistically significant decreases in the 24-hour urinary free cortisol levels compared to placebo.

Three clinical pharmacology studies have been conducted in pediatric patients to assess the effect of mometasone furoate nasal spray on the adrenal function at daily doses of 50, 100, and 200 mcg vs. placebo. In one study, adrenal function before and after 7 consecutive days of treatment was assessed in 48 pediatric patients with allergic rhinitis (ages 6 to 11 years) by measuring morning plasma cortisol and 24-hour urinary free cortisol levels. Mometasone furoate nasal spray, at all three doses, was not associated with a statistically significant decrease in mean plasma cortisol levels or a statistically significant decrease in the 24-hour urinary free cortisol levels compared to placebo. In the second study, adrenal function before and after 14 consecutive days of treatment was assessed in 48 pediatric patients (ages 3 to 5 years) with allergic rhinitis by measuring plasma cortisol levels following a 30-minute Cortrosyn infusion. Mometasone furoate nasal spray, 50 mcg, at all three doses (50, 100, and 200 mcg/day), was not associated with a statistically significant decrease in mean plasma cortisol levels post-Cortrosyn infusion compared to placebo. All patients had a normal response to Cortrosyn. In the third study, adrenal function before and after up to 42 consecutive days of once-daily treatment was assessed in 52 patients with allergic rhinitis (ages 2 to 5 years), 28 of whom received mometasone furoate nasal spray, 50 mcg per nostril (total daily dose 100 mcg), by measuring morning plasma cortisol and 24-hour urinary free cortisol levels. Mometasone furoate nasal spray was not associated with a statistically significant decrease in mean plasma cortisol levels or a statistically significant decrease in the 24-hour urinary free cortisol levels compared to placebo.

12.3 Pharmacokinetics

Absorption:

Mometasone furoate monohydrate administered as a nasal spray suspension has very low bioavailability (<1%) in plasma using a sensitive assay with a lower quantitation limit (LOQ) of 0.25 pcg/mL.

Distribution:

The in vitro protein binding for mometasone furoate was reported to be 98% to 99% in concentration range of 5 to 500 ng/mL.

Metabolism:

Studies have shown that any portion of a mometasone furoate dose which is swallowed and absorbed undergoes extensive metabolism to multiple metabolites. There are no major metabolites detectable in plasma. Upon in vitro incubation, one of the minor metabolites formed is 6ß-hydroxy-mometasone furoate. In human liver microsomes, the formation of the metabolite is regulated by cytochrome P-450 3A4 (CYP3A4).

Elimination:

Following intravenous administration, the effective plasma elimination half-life of mometasone furoate is 5.8 hours. Any absorbed drug is excreted as metabolites mostly via the bile, and to a limited extent, into the urine.

Specific Populations:

Hepatic Impairment: Administration of a single inhaled dose of 400 mcg mometasone furoate to subjects with mild (n=4), moderate (n=4), and severe (n=4) hepatic impairment resulted in only 1 or 2 subjects in each group having detectable peak plasma concentrations of mometasone furoate (ranging from 50 to 105 pcg/mL). The observed peak plasma concentrations appear to increase with severity of hepatic impairment, however, the numbers of detectable levels were few.

Renal Impairment: The effects of renal impairment on mometasone furoate pharmacokinetics have not been adequately investigated.

Pediatric: Mometasone furoate pharmacokinetics have not been investigated in the pediatric population [see Use in Specific Populations (8.4)].

Gender: The effects of gender on mometasone furoate pharmacokinetics have not been adequately investigated.

Race: The effects of race on mometasone furoate pharmacokinetics have not been adequately investigated.

Drug-Drug Interactions:

Inhibitors of Cytochrome P450 3A4: In a drug interaction study, an inhaled dose of mometasone furoate 400 mcg was given to 24 healthy subjects twice daily for 9 days and ketoconazole 200 mg (as well as placebo) were given twice daily concomitantly on Days 4 to 9. Mometasone furoate plasma concentrations were <150 pcg/mL on Day 3 prior to coadministration of ketoconazole or placebo. Following concomitant administration of ketoconazole, 4 out of 12 subjects in the ketoconazole treatment group (n=12) had peak plasma concentrations of mometasone furoate >200 pcg/mL on Day 9 (211–324 pcg/mL).

13. NONCLINICAL TOXICOLOGY

13.1 Carcinogenesis, Mutagenesis, Impairment of Fertility

In a 2-year carcinogenicity study in Sprague Dawley rats, mometasone furoate demonstrated no statistically significant increase in the incidence of tumors at inhalation doses up to 67 mcg/kg (approximately 1 and 2 times the maximum recommended daily intranasal dose [MRDID] in adults [400 mcg] and children [100 mcg], respectively, on a mcg/m^2 basis). In a 19-month carcinogenicity study in Swiss CD-1 mice, mometasone furoate demonstrated no statistically significant increase in the incidence of tumors at inhalation doses up to 160 mcg/kg (approximately 2 times the MRDID in adults and children, respectively, on a mcg/m^2 basis).

Mometasone furoate increased chromosomal aberrations in an in vitro Chinese hamster ovary-cell assay, but did not increase chromosomal aberrations in an in vitro Chinese hamster lung cell assay. Mometasone furoate was not mutagenic in the Ames test or mouse-lymphoma assay, and was not clastogenic in an in vivo mouse micronucleus assay and a rat bone marrow chromosomal aberration assay or a mouse male germ-cell chromosomal aberration assay. Mometasone furoate also did not induce unscheduled DNA synthesis in vivo in rat hepatocytes.

In reproductive studies in rats, impairment of fertility was not produced by subcutaneous doses up to 15 mcg/kg (less than the MRDID in adults on a mcg/m^2 basis).

13.2 Animal Toxicology and/or Pharmacology

Reproduction Toxicology Studies

In mice, mometasone furoate caused cleft palate at subcutaneous doses of 60 mcg/kg and above (less than the MRDID in adults on a mcg/m^2 basis). Fetal survival was reduced at 180 mcg/kg (approximately 2 times the MRDID in adults on a mcg/m^2 basis). No toxicity was observed at 20 mcg/kg (less than the MRDID in adults on a mcg/m^2 basis).

In rats, mometasone furoate produced umbilical hernia at topical dermal doses of 600 mcg/kg and above (approximately 10 times the MRDID in adults on a mcg/m^2 basis). A dose of 300 mcg/kg (approximately 6 times the MRDID in adults on a mcg/m^2 basis) produced delays in ossification, but no malformations. In rabbits, mometasone furoate caused multiple malformations (e.g., flexed front paws, gallbladder agenesis, umbilical hernia, hydrocephaly) at topical dermal doses of 150 mcg/kg and above (approximately 6 times the MRDID in adults on a mcg/m^2 basis). In an oral study, mometasone furoate increased resorptions and caused cleft palate and/or head malformations (hydrocephaly or domed head) at 700 mcg/kg (approximately 30 times the MRDID in adults on a mcg/m^2 basis). At 2800 mcg/kg (approximately 110 times the MRDID in adults on a mcg/m^2 basis), most litters were aborted or resorbed. No toxicity was observed at 140 mcg/kg (approximately 6 times the MRDID in adults on a mcg/m^2 basis).

When rats received subcutaneous doses of mometasone furoate throughout pregnancy or during the later stages of pregnancy, 15 mcg/kg (less than the MRDID in adults on a mcg/m^2 basis) caused prolonged and difficult labor and reduced the number of live births, birth weight, and early pup survival. Similar effects were not observed at 7.5 mcg/kg (less than the MRDID in adults on a mcg/m^2 basis).

14. CLINICAL STUDIES

14.1 Allergic Rhinitis in Adults and Adolescents

The efficacy and safety of NASONEX Nasal Spray, 50 mcg in the prophylaxis and treatment of seasonal allergic rhinitis and the treatment of perennial allergic rhinitis have been evaluated in 18 controlled trials, and one uncontrolled clinical trial, in approximately 3000 adults (ages 17 to 85 years) and adolescents (ages 12 to 16 years). Of the total number of patients, there were 1757 males and 1453 females, including a total of 283 adolescents (182 boys and 101 girls) with seasonal allergic or perennial allergic rhinitis. Patients were treated with NASONEX Nasal Spray 50 mcg at doses ranging from 50 to 800 mcg/day. The majority of patients were treated with 200 mcg/day. The allergic rhinitis trials evaluated the total nasal symptom scores that included stuffiness, rhinorrhea, itching, and sneezing. Patients treated with NASONEX Nasal Spray 50 mcg, 200 mcg/day had a statistically significant decrease in total nasal symptom scores compared to placebo-treated patients. No additional benefit was observed for mometasone furoate doses greater than 200 mcg/day. A total of 350 patients have been treated with NASONEX Nasal Spray 50 mcg for 1 year or longer.

In patients with seasonal allergic rhinitis, NASONEX Nasal Spray 50 mcg, demonstrated improvement in nasal symptoms (vs. placebo) within 11 hours after the first dose based on one single-dose, parallel-group study of patients in an outdoor "park" setting (park study) and one environmental exposure unit (EEU) study, and within 2 days in two randomized, double-blind, placebo-controlled, parallel-group seasonal allergic rhinitis studies. Maximum benefit is usually achieved within 1 to 2 weeks after initiation of dosing.

Prophylaxis of seasonal allergic rhinitis for patients 12 years of age and older with NASONEX Nasal Spray 50 mcg, given at a dose of 200 mcg/day, was evaluated in two clinical studies in 284 patients. These studies were designed such that patients received 4 weeks of prophylaxis with NASONEX Nasal Spray 50 mcg prior to the anticipated onset of the pollen season; however, some patients received only 2 to 3 weeks of prophylaxis. Patients receiving 2 to 4 weeks of prophylaxis with NASONEX Nasal Spray 50 mcg demonstrated a statistically significantly smaller mean increase in total nasal symptom scores with onset of the pollen season as compared to placebo patients.

14.2 Allergic Rhinitis in Pediatrics

The efficacy and safety of NASONEX Nasal Spray 50 mcg in the treatment of seasonal allergic and perennial allergic rhinitis in pediatric patients (ages 3 to 11 years) have been evaluated in four controlled trials. This included approximately 990 pediatric patients ages 3 to 11 years (606 males and 384 females) with seasonal allergic or perennial allergic rhinitis treated with mometasone furoate nasal spray at doses ranging from 25 to 200 mcg/day. Pediatric patients treated with NASONEX Nasal Spray 50 mcg (100 mcg total daily dose, 374 patients) had a significant decrease in total nasal symptom (nasal congestion, rhinorrhea, itching, and sneezing) scores, compared to placebo-treated patients. No additional benefit was observed for the 200-mcg mometasone furoate total daily dose in pediatric patients (ages 3 to 11 years). A total of 163 pediatric patients have been treated for 1 year.

14.3 Nasal Polyps in Adults 18 Years of Age and Older

Two studies were performed to evaluate the efficacy and safety of NASONEX Nasal Spray in the treatment of nasal polyps. These studies involved 664 patients with nasal polyps, 441 of whom received NASONEX Nasal Spray. These studies were randomized, double-blind, placebo-controlled, parallel-group, multicenter studies in patients 18 to 86 years of age with bilateral nasal polyps. Patients were randomized to receive NASONEX Nasal Spray 200 mcg once daily, 200 mcg twice daily or placebo for a period of 4 months. The co-primary efficacy endpoints were 1) change from baseline in nasal congestion/obstruction averaged over the first month of treatment; and 2) change from baseline to last assessment in bilateral polyp grade during the entire 4 months of treatment as assessed by endoscopy. Efficacy was demonstrated in both studies at a dose of 200 mcg twice daily and in one study at a dose of 200 mcg once a day (see TABLE 2 below).

TABLE 2: EFFECT OF NASONEX NASAL SPRAY IN TWO RANDOMIZED, PLACEBO-CONTROLLED TRIALS IN PATIENTS WITH NASAL POLYPS
 | NASONEX 200 mcg qd | NASONEX 200 mcg bid | Placebo | P value for NASONEX 200 mcg qd vs. placebo | P value for NASONEX 200 mcg bid vs. placebo
Study 1 | N=115 | N=122 | N=117
Baseline bilateral polyp grade [polyps in each nasal fossa were graded by the investigator based on endoscopic visualization, using a scale of 0–3 where 0 = no polyps; 1 = polyps in the middle meatus, not reaching below the inferior border of the middle turbinate; 2 = polyps reaching below the inferior border of the middle turbinate but not the inferior border of the inferior turbinate; 3 = polyps reaching to or below the border of the inferior turbinate, or polyps medial to the middle turbinate (score reflects sum of left and right nasal fossa grades).] | 4.21 | 4.27 | 4.25
Mean change from baseline in bilateral polyps grade | -1.15 | -0.96 | -0.50 | <0.001 | 0.01
Baseline nasal congestion [nasal congestion/obstruction was scored daily by the patient using a 0–3 categorical scale where 0 = no symptoms, 1 = mild symptoms, 2 = moderate symptoms and 3 = severe symptoms.] | 2.29 | 2.35 | 2.28
Mean change from baseline in nasal congestion | -0.47 | -0.61 | -0.24 | 0.001 | <0.001
Study 2 | N=102 | N=102 | N=106
Baseline bilateral polyp grade | 4.00 | 4.10 | 4.17
Mean change from baseline in bilateral polyps grade | -0.78 | -0.96 | -0.62 | 0.33 | 0.04
Baseline nasal congestion | 2.23 | 2.20 | 2.18
Mean change from baseline in nasal congestion | -0.42 | -0.66 | -0.23 | 0.01 | <0.001

There were no clinically relevant differences in the effectiveness of NASONEX Nasal Spray, 50 mcg, in the studies evaluating treatment of nasal polyps across subgroups of patients defined by gender, age, or race.

14.4 Nasal Congestion Associated with Seasonal Allergic Rhinitis

The efficacy and safety of NASONEX Nasal Spray 50 mcg for nasal congestion associated with seasonal allergic rhinitis were evaluated in three randomized, placebo-controlled, double blind clinical trials of 15 days duration. The three trials included a total of 1008 patients 12 years of age and older with nasal congestion associated with seasonal allergic rhinitis, of whom 506 received NASONEX Nasal Spray 200 mcg daily and 502 received placebo. Of the 1008 patients, the majority 784 (78 %) were Caucasians. The majority of the patients were between 18 to < 65 years of age with a mean age of 38.8 years and were predominantly women (66%). The primary efficacy endpoint was the change from baseline in average morning and evening reflective nasal congestion score over treatment day 1 to day 15. The key secondary efficacy endpoint was the change from baseline in average morning and evening reflective total nasal symptom score (TNSS = rhinorrhea [nasal discharge/runny nose or postnasal drip], nasal congestion/stuffiness, nasal itching, sneezing) averaged over treatment day 1 to 15. Two out of three studies demonstrated that treatment with Nasonex Nasal Spray significantly reduced the nasal congestion symptom score and the TNSS compared to placebo in patients 12 years of age and older with seasonal allergic rhinitis (see TABLE 3 and 4 below).

TABLE 3: EFFECT OF NASONEX NASAL SPRAY IN TWO RANDOMIZED, PLACEBO-CONTROLLED TRIALS ON NASAL CONGESTION IN PATIENTS WITH SEASONAL ALLERGIC RHINITIS
 | Treatment (Patient Number) | Baseline LS Mean [LS Mean and p- value was from an ANCOVA model with treatment, baseline value, and center effects.] | Change from Baseline LS Mean | Difference from Placebo LS Mean | P value for NASONEX 200 mcg qd vs. placebo
Study 1
 | NASONEX 200 mcg qd (N=176) | 2.63 | -0.64 | -0.15 | 0.006
 | Placebo (N=175) | 2.62 | -0.49
Study 2
 | NASONEX 200 mcg qd (N=168) | 2.62 | -0.71 | -0.31 | <0.001
 | Placebo (N=164) | 2.60 | -0.40

TABLE 4: EFFECT OF NASONEX NASAL SPRAY ON TNSS IN TWO RANDOMIZED, PLACEBO-CONTROLLED TRIALS IN PATIENTS WITH SEASONAL ALLERGIC RHINITIS
 | Treatment (Patient Number) | Baseline LS Mean [LS Mean and p- value was from an ANCOVA model with treatment, baseline value, and center effects.] | Change from Baseline LS Mean | Difference from Placebo LS Mean | P value for NASONEX 200 mcg qd vs. placebo
Study 1
 | NASONEX 200 mcg qd (N=176) | 9.60 | -2.68 | -0.83 | <0.001
 | Placebo (N=175) | 9.66 | -1.85
Study 2
 | NASONEX 200 mcg qd (N=168) | 9.39 | -3.00 | -1.27 | <0.001
 | Placebo (N=164) | 9.50 | -1.73

Based on results in other studies with NASONEX Nasal Spray in pediatric patients, effects on nasal congestion associated with seasonal allergic rhinitis in patients below 12 years of age is similar to those seen in adults and adolescents [see Clinical Studies (14.2)].

16. HOW SUPPLIED/STORAGE AND HANDLING

NASONEX (mometasone furoate monohydrate) Nasal Spray, 50 mcg is supplied in a white, high-density, polyethylene bottle fitted with a white metered-dose, manual spray pump, and blue cap. It contains 17 g of product formulation, 120 sprays, each delivering 50 mcg of mometasone furoate per actuation.

(NDC 54868-4174-0).

STORAGE AND HANDLING

Store at 25°C (77°F); excursions permitted to 15° to 30°C (59° to 86°F) [see USP Controlled Room Temperature]. Protect from light.

When NASONEX Nasal Spray, 50 mcg is removed from its cardboard container, prolonged exposure of the product to direct light should be avoided. Brief exposure to light, as with normal use, is acceptable.

SHAKE WELL BEFORE EACH USE.

Keep out of reach of children.

17. PATIENT COUNSELING INFORMATION

See FDA-approved labeling

17.1 Local Nasal Effect

Patients should be informed that treatment with NASONEX Nasal Spray 50 mcg may be associated with adverse reactions which include epistaxis (nose bleed) and nasal septum perforation. Candida infection may also occur. Because of the inhibitory effect of corticosteroids on wound healing, patients who have experienced recent nasal septum ulcers, nasal surgery, or nasal trauma should not use a nasal corticosteroid until healing has occurred [see Warnings and Precautions (5.1)]. Patients should be cautioned not to spray NASONEX Nasal Spray 50 mcg directly onto the nasal septum.

17.2 Glaucoma and Cataracts

Patients should be informed that nasal and inhaled corticosteroids may result in the development of glaucoma and/or cataracts. Therefore, close monitoring is warranted in patients with a change in vision or with a history of increased intraocular pressure, glaucoma, and/or cataracts. Patients should be cautioned not to spray NASONEX Nasal Spray 50 mcg into the eyes [see Warnings and Precautions (5.2)].

17.3 Immunosuppression

Persons who are on immunosuppressant doses of corticosteroids should be warned to avoid exposure to chickenpox or measles, and patients should also be advised that if they are exposed, medical advice should be sought without delay [see Warnings and Precautions (5.4)].

17.4 Use Regularly for Best Effect

Patients should use NASONEX Nasal Spray 50 mcg on a regular basis for optimal effect. Improvement in nasal symptoms of allergic rhinitis has been shown to occur within 1 to 2 days after initiation of dosing. Maximum benefit is usually achieved within 1 to 2 weeks after initiation of dosing. Patients should not increase the prescribed dosage but should contact their physician if symptoms do not improve, or if the condition worsens. Administration to young children should be aided by an adult.

If a patient missed a dose, the patient should be advised to take the dose as soon as they remember. The patient should not take more than the recommended dose for the day.

Schering Corporation, a subsidiary of (logo) MERCK & CO., INC., Whitehouse Station, NJ 08889, USA.

Copyright © 1997, 2010 Schering Corporation, a subsidiary of Merck & Co., Inc. All rights reserved.
U.S. Patent No. 6,127,353.
RevXX/XX

Relabeling of "Additional" barcode label by:
Physicians Total Care, Inc.
Tulsa, OK 74146

Patient Information

NASONEX® [nā-zə-neks] (mometasone furoate monohydrate) Nasal Spray, 50 mcg

FOR INTRANASAL USE ONLY

Read the Patient Information that comes with NASONEX before you start using it and each time you get a refill. There may be new information. This Patient Information does not take the place of talking to your health-care provider about your medical condition or treatment. If you have any questions about NASONEX, ask your health-care provider.

What is NASONEX?

NASONEX Nasal Spray is a man-made (synthetic) corticosteroid medicine that is used to:

- to treat the nasal symptoms of seasonal and year-round allergic rhinitis (inflammation of the lining of the nose) in adults and children 2 years of age and older.
- to treat nasal congestion that happens with seasonal allergic rhinitis in adults and children 2 years of age and older.
- to prevent nasal symptoms of seasonal allergic rhinitis in people 12 years of age and older.
- to treat nasal polyps in people 18 years and older.

The safety and effectiveness of NASONEX has not been shown:

- In children under 2 years of age to treat allergic rhinitis.
- In children under 18 years of age to treat nasal polyps.

Who should not use NASONEX?

Do not use NASONEX if you are allergic to any of the ingredients in NASONEX. See the end of this leaflet for a complete list of ingredients in NASONEX.

What should I tell my health-care provider before using NASONEX?

Before you take NASONEX, tell your health-care provider if you:

- have had recent nasal sores, nasal surgery, or nasal injury.
- have eye or vision problems, such as cataracts or glaucoma (increased pressure in your eye).
- have tuberculosis or any untreated fungal, bacterial, viral infections, or eye infections caused by herpes.
- have been near someone who has chickenpox or measles.
- are not feeling well or have any other symptoms that you do not understand.
- have any other medical conditions.
- are pregnant or planning to become pregnant. It is not known if NASONEX will harm your unborn baby. Talk to your doctor if you are pregnant or plan to become pregnant.
- are breast-feeding or planning to breast-feed. It is not known whether NASONEX passes into your breast milk.

Tell your health-care provider about all the medicines you take including prescription and non-prescription medicines, vitamins, and herbal supplements.

NASONEX and other medicines may affect each other and cause side effects. NASONEX may affect the way other medicines work, and other medicines may affect how NASONEX works.

Know the list of medicine you take. Keep a list of your medications with you to show your health-care provider and pharmacist when a new medication is prescribed.

How should I use NASONEX?

- Use NASONEX exactly as prescribed by your health-care provider.
- This medicine is for use in the nose only. Do not spray it into your mouth or eyes.
- An adult should help a young child use this medicine.
- For best results, you should keep using NASONEX regularly each day without missing a dose. If you do miss a dose of NASONEX, take it as soon as you remember. However, do not take more than the daily dose prescribed by your doctor.
- Do not use NASONEX more often than prescribed. Ask your health-care provider if you have any questions.
- For detailed instructions on how to use NASONEX Nasal Spray, see the "Patient's Instructions for Use" at the end of this leaflet.

See your health-care provider regularly to assess your symptoms while taking NASONEX and to check for side effects.

What should I avoid while taking NASONEX?

If you are taking other corticosteroid medicines for allergy, either by mouth or injection, your health-care provider may advise you to stop taking them once you begin using NASONEX.

What are the possible side effects of NASONEX?

NASONEX may cause serious side effects, including:

- Thrush (candida), a fungal infection in your nose and throat. Tell your doctor if you have any redness or white colored patches in your nose or throat.
- Slow wound healing. Do not use NASONEX until your nose has healed if you have a sore in your nose, if you have surgery on your nose, or if your nose has been injured.
- Some people may have eye problems, including glaucoma and cataracts. You should have regular eye exams.
- Immune system problems that may increase your risk of infections. You are more likely to get infections if you take medicines that weaken your immune system. Avoid contact with people who have contagious diseases such as chicken pox or measles while using NASONEX. Symptoms of infection may include: fever, pain, aches, chills, feeling tired, nausea and vomiting. Tell your doctor about any signs of infection while you are using NASONEX.
- Adrenal insufficiency. Adrenal insufficiency is a condition in which the adrenal glands do not make enough steroid hormones. Symptoms of adrenal insufficiency can include: tiredness, weakness, nausea and vomiting and low blood pressure.

The most common side effects of NASONEX include:

- Headache
- viral infection
- sore throat
- nosebleeds
- cough

Tell your health-care provider if you have any side effect that bothers you or that does not go away.

These are not all the possible side effects of NASONEX. For more information ask your health-care provider or pharmacist.

Call your doctor for medical advice about side effects. You may report side effects to FDA at 1-800-FDA-1088.

How should I store NASONEX?

- Store NASONEX at room temperature between 59°F to 86°F (15°C to 30°C).
- Avoid prolonged exposure NASONEX container to bright light.
- Shake well before each use.

Keep NASONEX and all medicines out of the reach of children.

General information about NASONEX

Medicines are sometimes prescribed for conditions that are not listed in a Patient Information leaflet. Do not use NASONEX for a condition for which it was not prescribed. Do not give NASONEX to other people even if they have the same symptoms you have. It may harm them.

This Patient Information leaflet provides a summary of the most important information about NASONEX. If you would like more information, talk with your health-care provider. You can ask your health-care provider or pharmacist for information about NASONEX that is written for health professionals.

For more information, go to www.NASONEX.com or call 1-800-526-4099.

What are the ingredients in NASONEX?

Active Ingredients: mometasone furoate monohydrate

Inactive Ingredients: glycerin, microcrystalline cellulose and carboxymethycellulose sodium, sodium citrate, citric acid, benzalkonium chloride, and polysorbate 80.

Patient Instructions for Use

For use in your nose only.

Read the Patient Instructions for Use carefully before you start to use your NASONEX Nasal Spray. If you have any questions, ask your health-care provider.

Shake the bottle well before each use.

1. Remove the plastic cap (Figure 1).

2. Before you use NASONEX for the first time prime the pump by pressing downward on the shoulders of the white nasal applicator using your index finger and middle finger while holding the base of the bottle with your thumb (Figure 2). Do Not pierce the nasal applicator. Press down and release the pump 10 times or until a fine spray appears. Do Not spray into eyes. The pump is now ready to use. The pump may be stored unused for up to 1 week without repriming. If unused for more than 1 week, reprime by spraying 2 times or until a fine spray appears.

3. Gently blow your nose to clear the nostrils. Close 1 nostril. Tilt your head forward slightly, keep the bottle upright, carefully insert the nasal applicator into the other nostril (Figure 3). Do Not spray directly onto the nasal septum (the wall between the two nostrils).

4. For each spray, hold the spray bottle upright and press firmly downward 1 time on the shoulders of the white nasal applicator using your index and middle fingers while supporting the base of the bottle with your thumb. Breathe gently inward through the nostril (Figure 4).

Note: It is important to keep the Nasonex unit in an upright orientation (as seen in Figure 4). Failure to do so may result in an incomplete or non-existent spray.

5. Then breathe out through the mouth.

6. Repeat in the other nostril.

7. Wipe the nasal applicator with a clean tissue and replace the plastic cap.

Each bottle of NASONEX Nasal Spray contains enough medicine for you to spray medicine from the bottle 120 times. Do not use the bottle of NASONEX Nasal Spray after 120 sprays. Additional sprays after the 120 sprays may not contain the right amount of medicine, you should keep track of the number of sprays used from each bottle of NASONEX Nasal Spray, and throw away the bottle even if it has medicine still left in. Do not count any sprays used for priming the device. Talk with your health-care provider before your supply runs out to see if you should get a refill of your medicine.

Pediatric Use: Administration to young children should be done by an adult. Steps 1 through 7 from the Patient Instructions for Use, should be followed.

Cleaning: Do not try to unblock the nasal applicator with a sharp object. Please see Applicator Cleaning Instructions.

Patient Instruction for cleaning applicator

1. To clean the nasal applicator, remove the plastic cap (Figure 5).

2. Pull gently upward on the white nasal applicator to remove (Figure 6).

3. Soak the nasal applicator in cold tap water and rinse both ends of the nasal applicator under cold tap water and dry. (Figure 7). Do not try to unblock the nasal applicator by inserting a pin or other sharp object as this will damage the applicator and cause you not to get the right dose of medicine.

4. Rinse the plastic cap under cold water and dry (Figure 8).

5. Put the nasal applicator back together making sure the pump stem is reinserted into the applicator's center hole (Figure 9).

6. Reprime the pump by pressing downward on the shoulders of the white nasal applicator using your index and middle fingers while holding the base of the bottle with your thumb. Press down and release the pump 2 times or until a fine spray appears. Do Not spray into eyes. The pump is now ready to use. The pump may be stored unused for up to 1 week without repriming. If unused for more than 1 week, reprime by spraying 2 times or until a fine spray appears (Figure 10).

7. Replace the plastic cap (Figure 11).

Schering Corporation, a subsidiary of (logo) MERCK & CO., INC., Whitehouse Station, NJ 08889, USA.

Copyright © 1997, 2010 Schering Corporation, a subsidiary of Merck & Co., Inc. All rights reserved.
U.S. Patent No. 6,127,353.
Rev. XX/XX
XXXXXXX

PACKAGE LABEL

PRINCIPAL DISPLAY PANEL - 17 g Carton

NDC 54868-4174-0

Scent-Free Mist

Net Contents: 17 g

120 Metered Sprays

For Intranasal Use Only

Rx Only

For more NASONEX® information log on to
www.nasonex.com